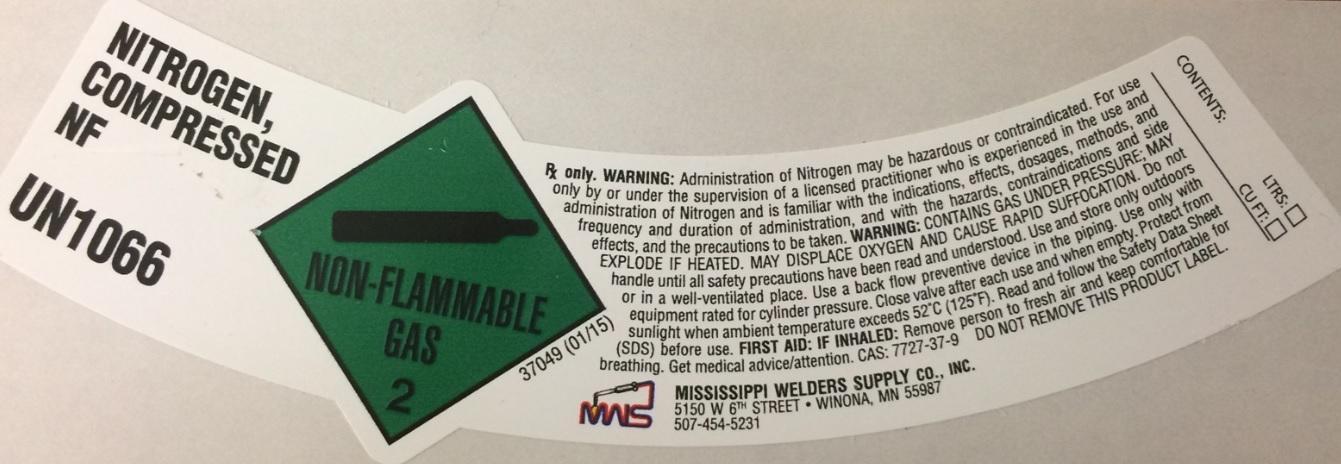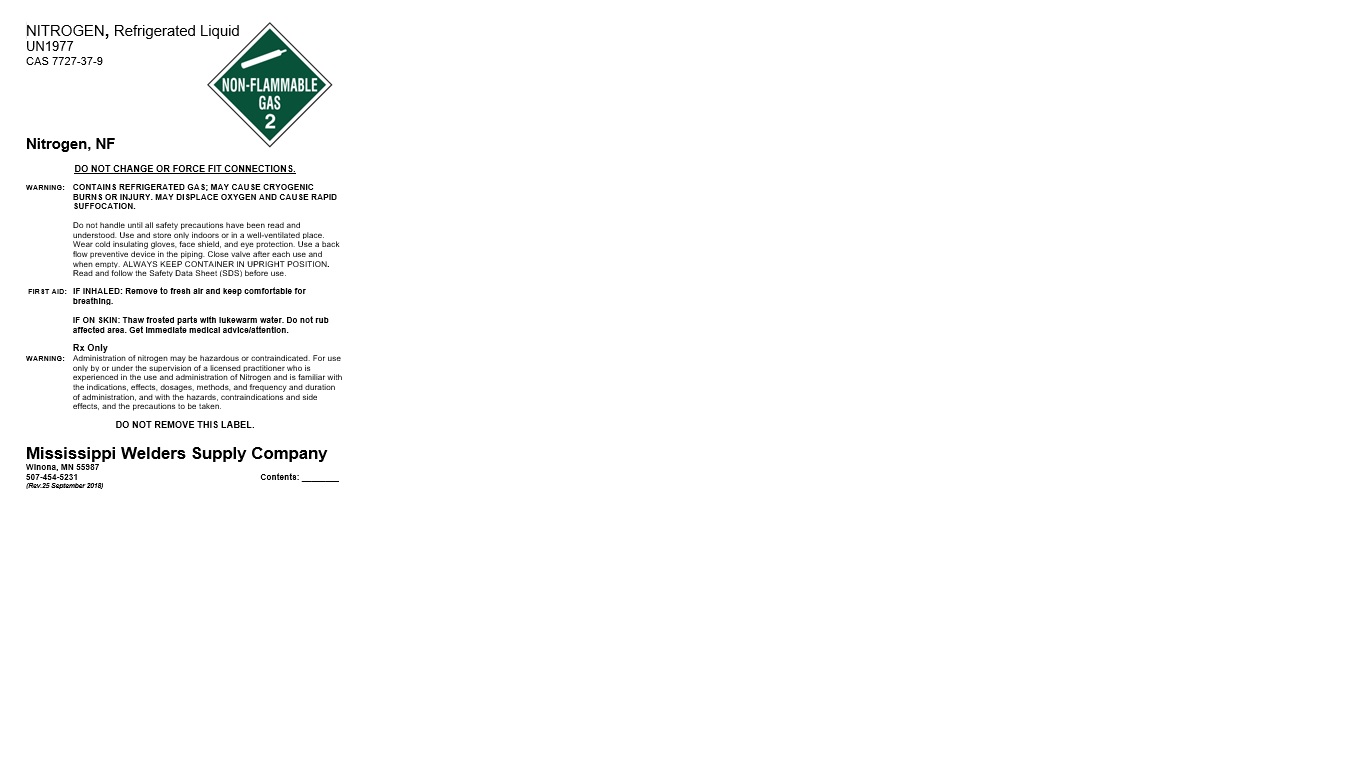 DRUG LABEL: Nitrogen
NDC: 51996-003 | Form: GAS
Manufacturer: Mississippi Welders Supply Company, Inc.
Category: prescription | Type: HUMAN PRESCRIPTION DRUG LABEL
Date: 20251125

ACTIVE INGREDIENTS: NITROGEN 990 mL/1 L

nitrogen

PACKAGE LABEL

NITROGEN, Refrigerated Liquid
UN1977
CAS 7727-37-9

Nitrogen, NF

DO NOT CHANGE OR FORCE FIT CONNECTIONS.

WARNING: CONTAINS REFRIGERATED GAS; MAY CAUSE CRYOGENIC BURNS OR INJURY. MAY DISPLACE OXYGEN AND CAUSE RAPID SUFFOCATION.

Do not handle until all safety precautions have been read and understood. Use and store only indoors or in a well-ventilated place. Wear cold insulating gloves, face shield, and eye protection. Use a back flow preventive device in the piping. Close valve after each use and when empty. ALWAYS KEEP CONTAINER IN UPRIGHT POSITION. Read and follow the Safety Data Sheet (SDS) before use.

FIRST AID: IF INHALED: Remove to fresh air and keep comfortable for breathing.

IF ON SKIN: Thaw frosted parts with lukewarm water. Do not rub affected area. Get immediate medical advice/attention.

Rx Only
WARNING: Administration of nitrogen may be hazardous or contraindicated. For use only by or under the supervision of a licensed practitioner who is experienced in the use and administration of Nitrogen and is familiar with the indications, effects, dosages, methods, and frequency and duration of administration, and with the hazards, contraindications and side effects, and the precautions to be taken.

DO NOT REMOVE THIS LABEL.

Mississippi Welders Supply Company
Winona, MN 55987
507-454-5231 Contents: ________
(Rev.25 September 2018)

PACKAGE LABEL

NITROGEN, COMPRESSED,NF
UN1066

NON-FLAMMABLE GAS 2

Rx only. WARNING: Administration of Nitrogen may be hazardous or contraindicated. For use only by or under the supervision of a licensed practitioner who is experienced in the use and administration of Nitrogen and is familiar with the indications, effects, dosages, methods, and frequency and duration of administration, and with the hazards, contraindications and side effects, and the precautions to be taken. WARNING: CONTAINS GAS UNDER PRESSURE MAY EXPLODE IF HEATED. MAY DISPLACE OXYGEN AND CAUSE RAPID SUFFOCATION. Do not handle until all safety precautions have been read and understood. Use and store only outdoors or in a well-ventilated place. Use a back flow preventive device in the piping. Use only with equipment rated for cylinder pressure. Close valve after each use and when empty. Protect from sunlight when ambient temperature exceeds 52 degrees C (125 degrees F). Read and follow the Safety Data Sheet (SDS) before use. FIRST AID: IF INHALED: Remove person to fresh air and keep comfortable for breathing. Get medical advice/attentions. CAS: 7727-37-9. DO NOT REMOVE THIS PRODUCT LABEL.

MISSISSIPPI WELDERS SUPPLY CO., INC.
5150 W 6TH STREET, WINONA, MN 55987
507-454-5231

CONTENTS: LTRS:
CU. FT.: